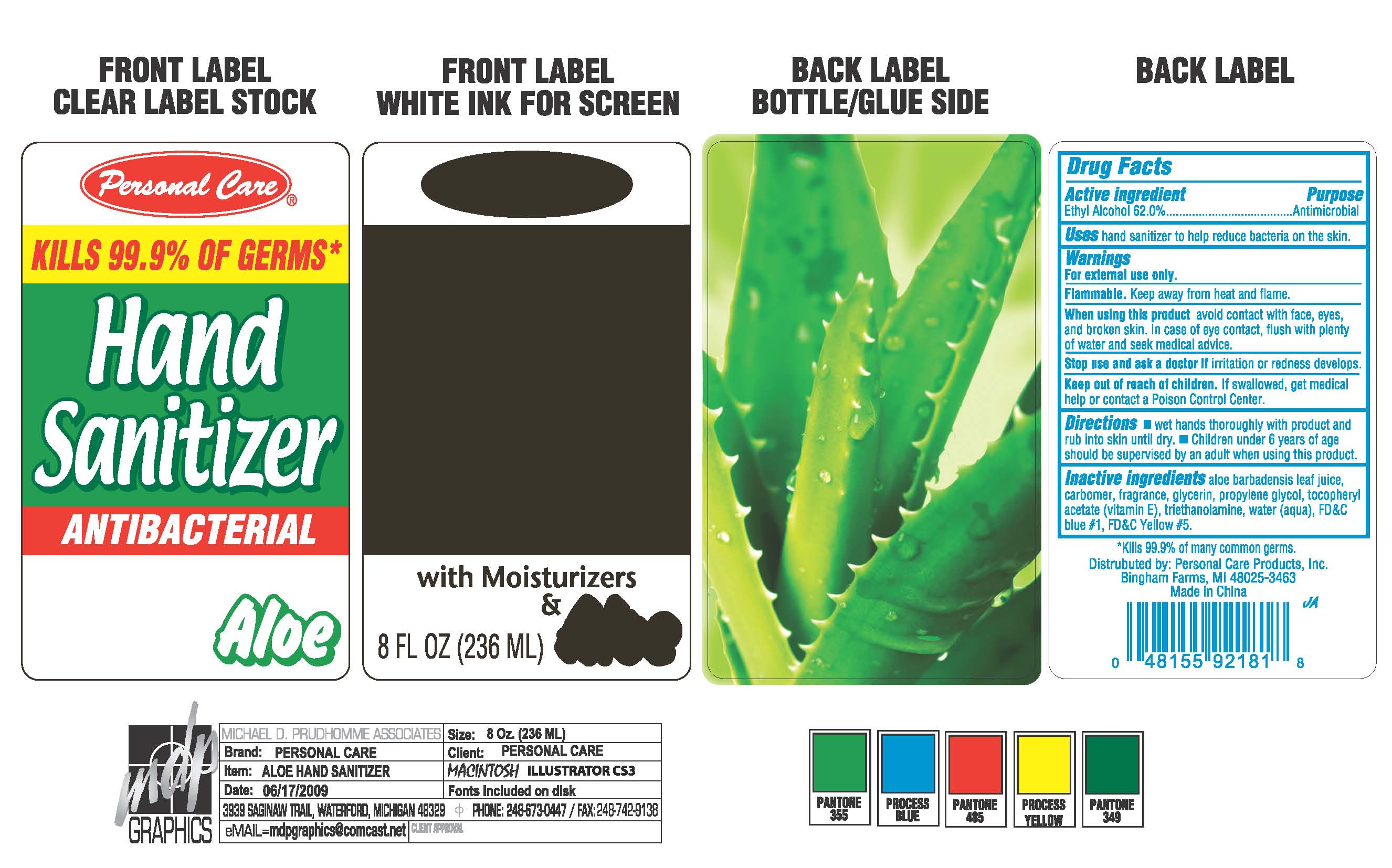 DRUG LABEL: Personal Care
                        
NDC: 29500-9080 | Form: GEL
Manufacturer: Personal Care Products, Inc.
Category: otc | Type: HUMAN OTC DRUG LABEL
Date: 20110825

ACTIVE INGREDIENTS: ALCOHOL 0.62 mL/1 mL
INACTIVE INGREDIENTS: ALOE VERA LEAF; CARBOMER HOMOPOLYMER TYPE C; GLYCERIN; PROPYLENE GLYCOL; ALPHA-TOCOPHEROL ACETATE; TROLAMINE; WATER; FD&C BLUE NO. 1; FD&C YELLOW NO. 5

Personal Care Hand Sanitizer

Active Ingredient Purpose

Ethyl Alcohol 62 percent Antimicrobial

Uses

hand sanitizer to help reduce bacteria on the skin.

Warnings

For external use only.

SAFE HANDLING WARNING

Flammable

Keep away from heat and flame.

When using this product avoid contact with face, eyes,

and broken skin. In case of eye contact, flush with plenty

of water and seek medical advice.

Stop use and ask a doctor if irritation or redness develops.

Keep out of reach of children. If swallowed, get medical help or contact a Poison Control Center.

Directions

wet hands thoroughly with product and rub into skin until dry.

Children under 6 years of age should be supervised by an adult when using this product.

Inactive ingredients

aloe barbadensis leaf juice,

carbomer, fragrance, glycerin, propylene glycol , tocopheryl acetate vitamin E,

triethanolamine, water aqua, FD and C blue 1, FD and C Yellow 5

Uses
Hand sanitizer to reduce bacteria on the skin

Directions

Wet hands thoroughly with product and rub into skin until dry. Children under 6 years of age should be supervised by an adult when using this product.

PACKAGE LABEL

Personal Care

Kills 99.9%* of germs

Hand Sanitizer

Antibacterial

With Moisterizers and Aloe

8 fl oz (236 ml)